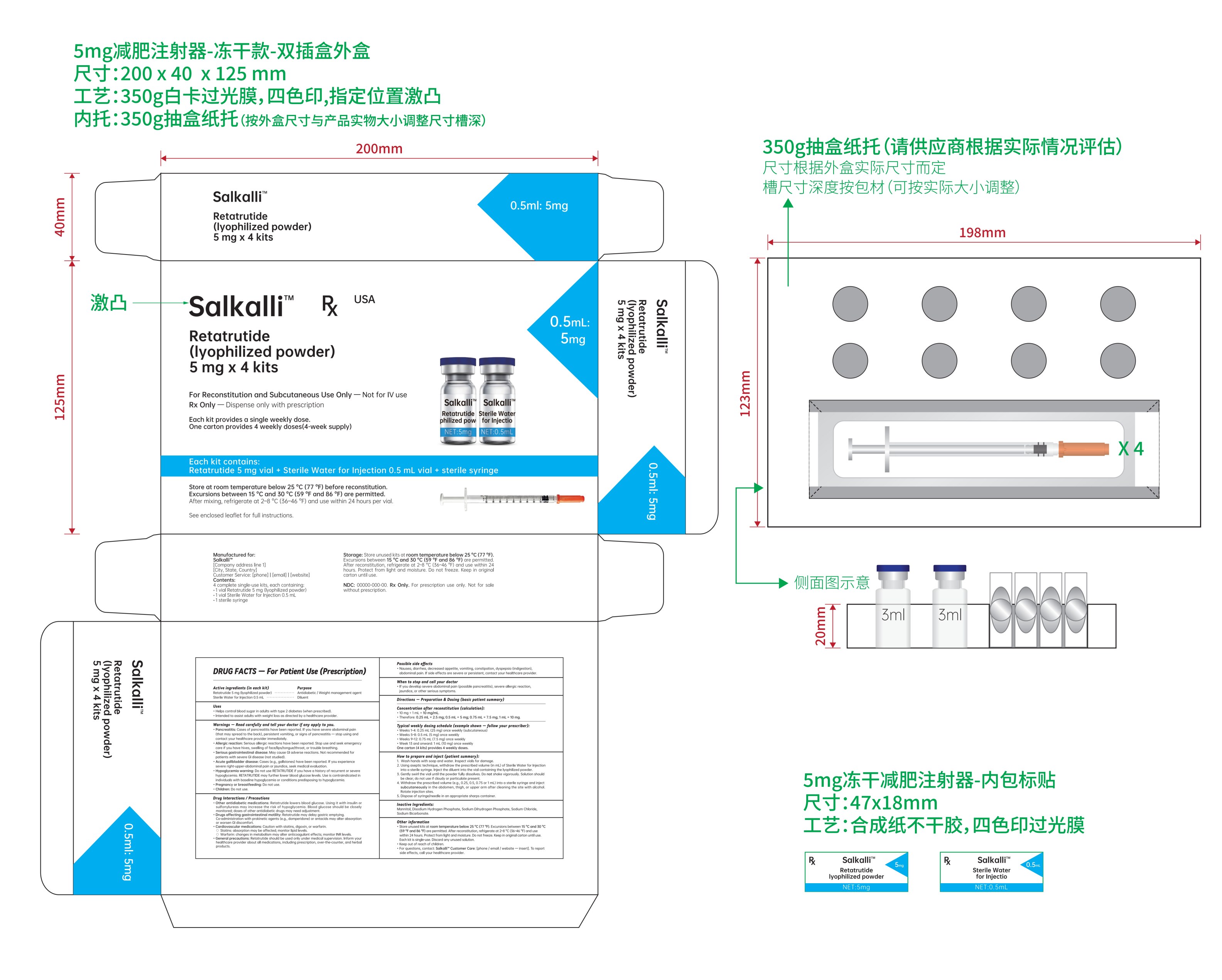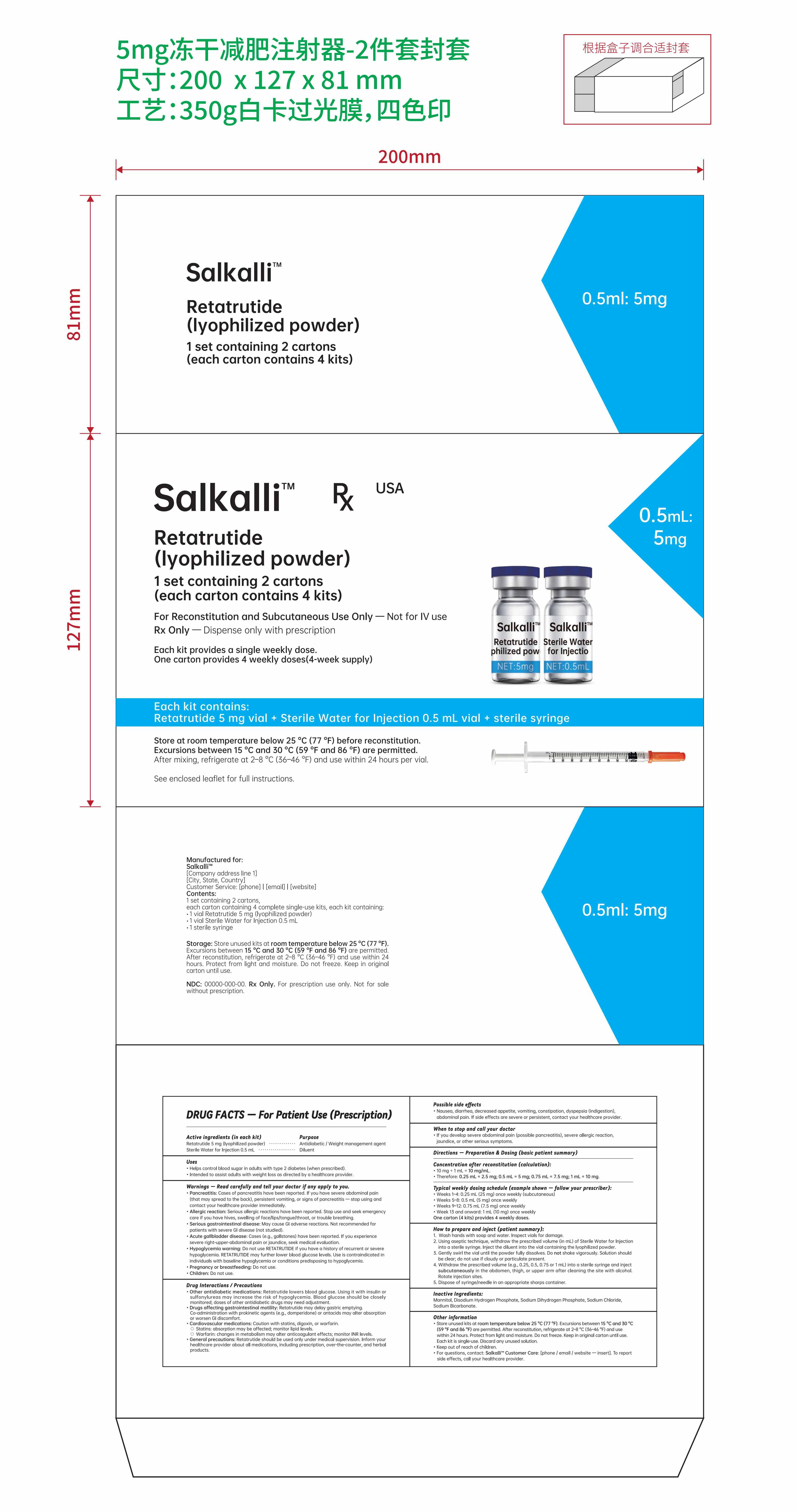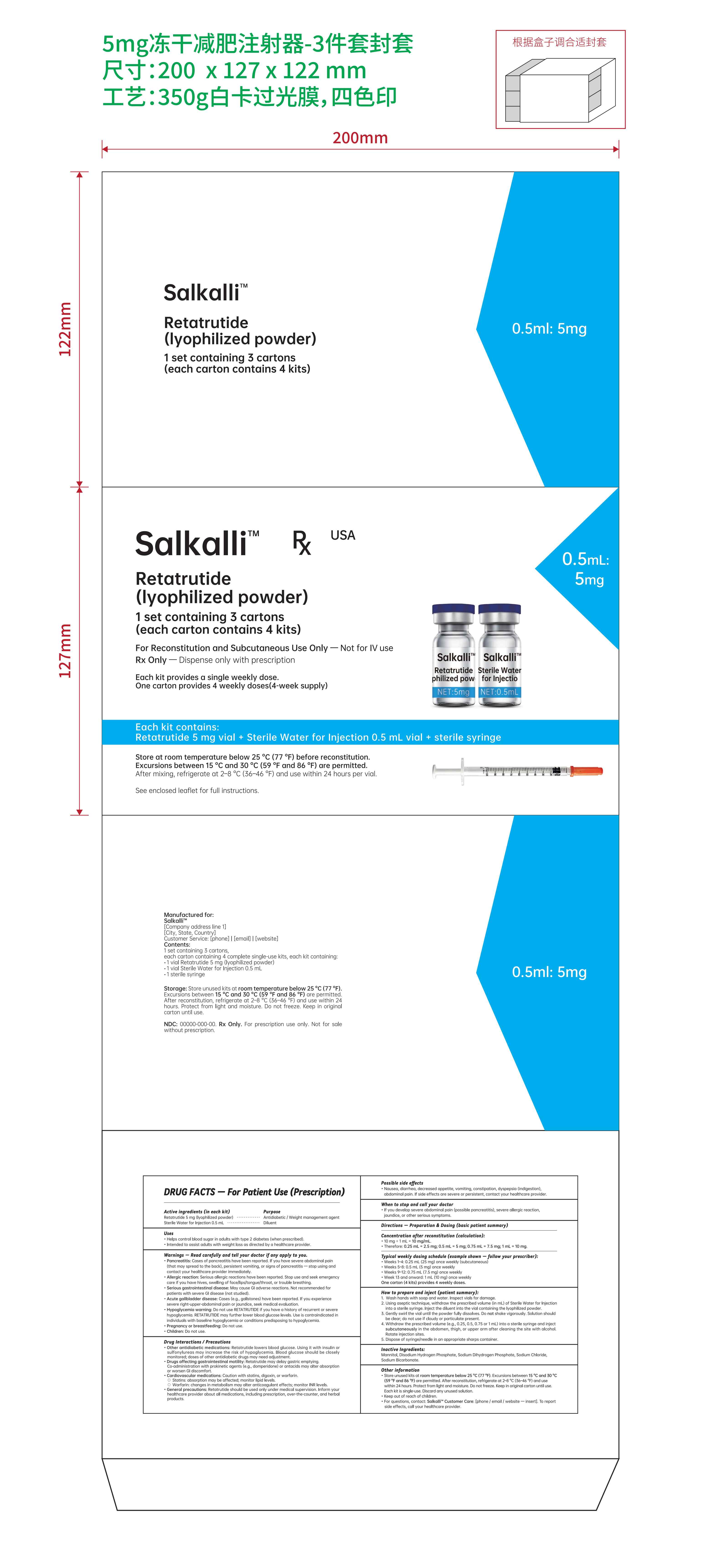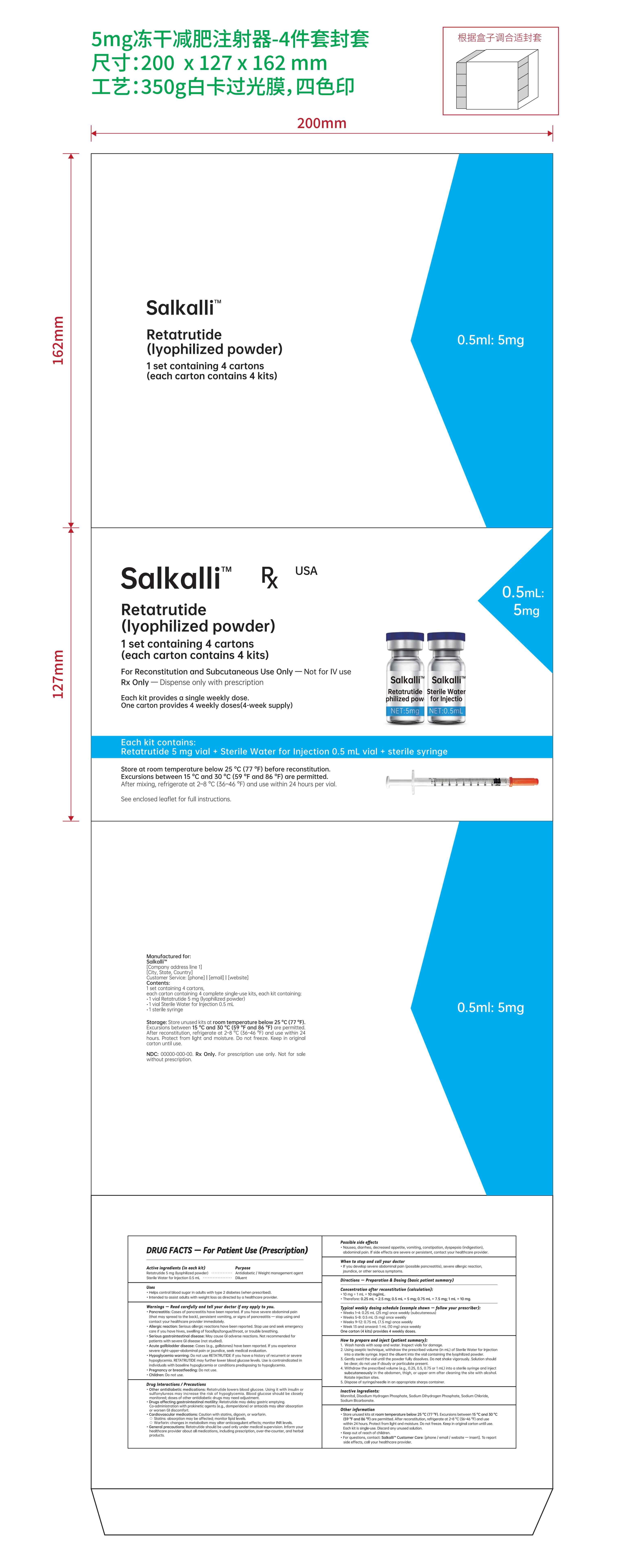 DRUG LABEL: Salkalli
NDC: 84778-113 | Form: INJECTION, POWDER, LYOPHILIZED, FOR SOLUTION
Manufacturer: Guangzhou Yixin Cross-border E-commerce Co., Ltd.
Category: prescription | Type: HUMAN PRESCRIPTION DRUG LABEL
Date: 20251107

ACTIVE INGREDIENTS: RETATRUTIDE 5 mg/0.5 mL
INACTIVE INGREDIENTS: SODIUM BICARBONATE; MANNITOL; SODIUM PHOSPHATE, MONOBASIC, UNSPECIFIED FORM; SODIUM PHOSPHATE, DIBASIC, ANHYDROUS; SODIUM CHLORIDE

Active ingredients (in each kit)

Retatrutide 5 mg (lyophilized powder)

Sterile Water for Injection 0.5 mL

Purpose

Antidiabetic / Weight management agent

Diluent

Uses

Helps control blood sugar in adults with type 2 diabetes (when prescribed).
Intended to assist adults with weight loss as directed by a healthcare provider.

Warnings — Read carefully and tell your doctor if any apply to you.

Pancreatitis: Cases of pancreatitis have been reported. If you have severe abdominal pain (that may spread to the back), persistent vomiting, or signs of pancreatitis — stop using and contact your healthcare provider immediately.
Allergic reaction: Serious allergic reactions have been reported. Stop use and seek emergency care if you have hives, swelling of face/lips/tongue/throat, or trouble breathing.
Serious gastrointestinal disease: May cause GI adverse reactions. Not recommended for patients with severe GI disease (not studied).
Acute gallbladder disease: Cases (e.g., gallstones) have been reported. If you experience severe right-upper-abdominal pain or jaundice, seek medical evaluation.
Hypoglycemia warning: Do not use RETATRUTIDE if you have a history of recurrent or severe hypoglycemia. RETATRUTIDE may further lower blood glucose levels. Use is contraindicated in individuals with baseline hypoglycemia or conditions predisposing to hypoglycemia.
Pregnancy or breastfeeding: Do not use.
Children: Do not use.

Drug Interactions / Precautions

Other antidiabetic medications: Retatrutide lowers blood glucose. Using it with insulin or sulfonylureas may increase the risk of hypoglycemia. Blood glucose should be closely monitored; doses of other antidiabetic drugs may need adjustment.
Drugs affecting gastrointestinal motility: Retatrutide may delay gastric emptying. Co-administration with prokinetic agents (e.g., domperidone) or antacids may alter absorption or worsen GI discomfort.
Cardiovascular medications: Caution with statins, digoxin, or warfarin.

Statins: absorption may be affected; monitor lipid levels.
Warfarin: changes in metabolism may alter anticoagulant effects; monitor INR levels.

General precautions: Retatrutide should be used only under medical supervision. Inform your healthcare provider about all medications, including prescription, over-the-counter, and herbal products.

Possible side effects

Nausea, diarrhea, decreased appetite, vomiting, constipation, dyspepsia (indigestion), abdominal pain. If side effects are severe or persistent, contact your healthcare provider.

When to stop and call your doctor

If you develop severe abdominal pain (possible pancreatitis), severe allergic reaction, jaundice, or other serious symptoms.

Directions — Preparation & Dosing (basic patient summary)

Concentration after reconstitution (calculation):

10 mg ÷ 1 mL = 10 mg/mL.
Therefore: 0.25 mL = 2.5 mg; 0.5 mL = 5 mg; 0.75 mL = 7.5 mg; 1 mL = 10 mg.

Typical weekly dosing schedule (example shown — follow your prescriber):

Weeks 1–4: 0.25 mL (2.5 mg) once weekly (subcutaneous)
Weeks 5–8: 0.5 mL (5 mg) once weekly
Weeks 9–12: 0.75 mL (7.5 mg) once weekly
Week 13 and onward: 1 mL (10 mg) once weekly

One carton (4 kits) provides 4 weekly doses.

How to prepare and inject (patient summary):

Wash hands with soap and water. Inspect vials for damage.
Using aseptic technique, withdraw the prescribed volume (in mL) of Sterile Water for Injection into a sterile syringe. Inject the diluent into the vial containing the lyophilized powder.
Gently swirl the vial until the powder fully dissolves. Do not shake vigorously. Solution should be clear; do not use if cloudy or particulate present.
Withdraw the prescribed volume (e.g., 0.25, 0.5, 0.75 or 1 mL) into a sterile syringe and inject subcutaneously in the abdomen, thigh, or upper arm after cleaning the site with alcohol. Rotate injection sites.
Dispose of syringe/needle in an appropriate sharps container.

Do not use

Other antidiabetic medications: Retatrutide lowers blood glucose. Using it with insulin or sulfonylureas may increase the risk of hypoglycemia. Blood glucose should be closely monitored; doses of other antidiabetic drugs may need adjustment.
Drugs affecting gastrointestinal motility: Retatrutide may delay gastric emptying. Co-administration with prokinetic agents (e.g., domperidone) or antacids may alter absorption or worsen GI discomfort.
Cardiovascular medications: Caution with statins, digoxin, or warfarin.

Statins: absorption may be affected; monitor lipid levels.
Warfarin: changes in metabolism may alter anticoagulant effects; monitor INR levels.

General precautions: Retatrutide should be used only under medical supervision. Inform your healthcare provider about all medications, including prescription, over-the-counter, and herbal products.

When using section

Pancreatitis: Cases of pancreatitis have been reported. If you have severe abdominal pain (that may spread to the back), persistent vomiting, or signs of pancreatitis — stop using and contact your healthcare provider immediately.
Allergic reaction: Serious allergic reactions have been reported. Stop use and seek emergency care if you have hives, swelling of face/lips/tongue/throat, or trouble breathing.
Serious gastrointestinal disease: May cause GI adverse reactions. Not recommended for patients with severe GI disease (not studied).
Acute gallbladder disease: Cases (e.g., gallstones) have been reported. If you experience severe right-upper-abdominal pain or jaundice, seek medical evaluation.
Hypoglycemia warning: Do not use RETATRUTIDE if you have a history of recurrent or severe hypoglycemia. RETATRUTIDE may further lower blood glucose levels. Use is contraindicated in individuals with baseline hypoglycemia or conditions predisposing to hypoglycemia.
Pregnancy or breastfeeding: Do not use.
Children: Do not use.

Drug Interactions / Precautions

Other antidiabetic medications: Retatrutide lowers blood glucose. Using it with insulin or sulfonylureas may increase the risk of hypoglycemia. Blood glucose should be closely monitored; doses of other antidiabetic drugs may need adjustment.
Drugs affecting gastrointestinal motility: Retatrutide may delay gastric emptying. Co-administration with prokinetic agents (e.g., domperidone) or antacids may alter absorption or worsen GI discomfort.
Cardiovascular medications: Caution with statins, digoxin, or warfarin.

Statins: absorption may be affected; monitor lipid levels.
Warfarin: changes in metabolism may alter anticoagulant effects; monitor INR levels.

General precautions: Retatrutide should be used only under medical supervision. Inform your healthcare provider about all medications, including prescription, over-the-counter, and herbal products.

Possible side effects

Nausea, diarrhea, decreased appetite, vomiting, constipation, dyspepsia (indigestion), abdominal pain. If side effects are severe or persistent, contact your healthcare provider.

When to stop and call your doctor

If you develop severe abdominal pain (possible pancreatitis), severe allergic reaction, jaundice, or other serious symptoms.

stop use

Pancreatitis: Cases of pancreatitis have been reported. If you have severe abdominal pain (that may spread to the back), persistent vomiting, or signs of pancreatitis — stop using and contact your healthcare provider immediately.
Allergic reaction: Serious allergic reactions have been reported. Stop use and seek emergency care if you have hives, swelling of face/lips/tongue/throat, or trouble breathing.
Serious gastrointestinal disease: May cause GI adverse reactions. Not recommended for patients with severe GI disease (not studied).
Acute gallbladder disease: Cases (e.g., gallstones) have been reported. If you experience severe right-upper-abdominal pain or jaundice, seek medical evaluation.
Hypoglycemia warning: Do not use RETATRUTIDE if you have a history of recurrent or severe hypoglycemia. RETATRUTIDE may further lower blood glucose levels. Use is contraindicated in individuals with baseline hypoglycemia or conditions predisposing to hypoglycemia.
Pregnancy or breastfeeding: Do not use.
Children: Do not use.

Drug Interactions / Precautions

Other antidiabetic medications: Retatrutide lowers blood glucose. Using it with insulin or sulfonylureas may increase the risk of hypoglycemia. Blood glucose should be closely monitored; doses of other antidiabetic drugs may need adjustment.
Drugs affecting gastrointestinal motility: Retatrutide may delay gastric emptying. Co-administration with prokinetic agents (e.g., domperidone) or antacids may alter absorption or worsen GI discomfort.
Cardiovascular medications: Caution with statins, digoxin, or warfarin.

Statins: absorption may be affected; monitor lipid levels.
Warfarin: changes in metabolism may alter anticoagulant effects; monitor INR levels.

General precautions: Retatrutide should be used only under medical supervision. Inform your healthcare provider about all medications, including prescription, over-the-counter, and herbal products.

Possible side effects

Nausea, diarrhea, decreased appetite, vomiting, constipation, dyspepsia (indigestion), abdominal pain. If side effects are severe or persistent, contact your healthcare provider.

When to stop and call your doctor

If you develop severe abdominal pain (possible pancreatitis), severe allergic reaction, jaundice, or other serious symptoms.

Keep out of reach of children.

Not for use in children.

Inactive Ingredients:

Mannitol, Disodium Hydrogen Phosphate, Sodium Dihydrogen Phosphate, Sodium Chloride, Sodium Bicarbonate.